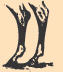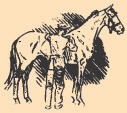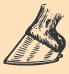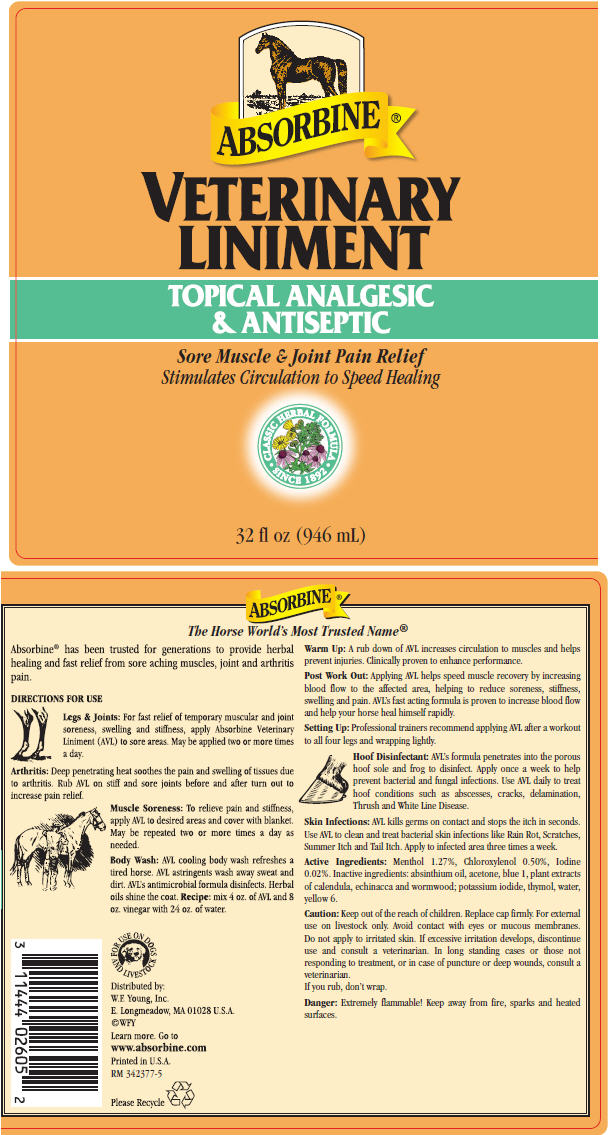 DRUG LABEL: Absorbine Veterinary
NDC: 11444-026 | Form: LIQUID
Manufacturer: W. F. Young, Inc.
Category: animal | Type: OTC ANIMAL DRUG LABEL
Date: 20241101

ACTIVE INGREDIENTS: MENTHOL, UNSPECIFIED FORM 1.27 g/100 mL; CHLOROXYLENOL 0.5 g/100 mL; IODINE 0.02 g/100 mL
INACTIVE INGREDIENTS: ACETONE; FD&C BLUE NO. 1; FD&C YELLOW NO. 6; POTASSIUM IODIDE; THYMOL; CALENDULA OFFICINALIS FLOWER; ECHINACEA, UNSPECIFIED; WORMWOOD; WATER

ABSORBINE ®
VETERINARY
LINIMENT

VETERINARY INDICATIONS

Absorbine® has been trusted for generations to provide herbal healing and fast relief from sore aching muscles, joint and arthritis pain.

DIRECTIONS FOR USE

Legs & Joints

For fast relief of temporary muscular and joint soreness, swelling and stiffness, apply Absorbine Veterinary Liniment (AVL) to sore areas. May be applied two or more times a day.

Arthritis

Deep penetrating heat soothes the pain and swelling of tissues due to arthritis. Rub AVL on stiff and sore joints before and after turn out to increase pain relief.

Muscle Soreness

To relieve pain and stiffness, apply AVL to desired areas and cover with blanket. May be repeated two or more times a day as needed.

Body Wash

AVL cooling body wash refreshes a tired horse. AVL astringents wash away sweat and dirt. AVL's antimicrobial formula disinfects. Herbal oils shine the coat. Recipe: mix 4 oz. of AVL and 8 oz. vinegar with 24 oz. of water.

Warm Up

A rub down of AVL increases circulation to muscles and helps prevent injuries. Clinically proven to enhance performance.

Post Work Out

Applying AVL helps speed muscle recovery by increasing blood flow to the affected area, helping to reduce soreness, stiffness, swelling and pain. AVL's fast acting formula is proven to increase blood flow and help your horse heal himself rapidly.

Setting Up

Professional trainers recommend applying AVL after a workout to all four legs and wrapping lightly.

Hoof Disinfectant

AVL's formula penetrates into the porous hoof sole and frog to disinfect. Apply once a week to help prevent bacterial and fungal infections. Use AVL daily to treat hoof conditions such as abscesses, cracks, delamination, Thrush and White Line Disease.

Skin Infections

AVL kills germs on contact and stops the itch in seconds. Use AVL to clean and treat bacterial skin infections like Rain Rot, Scratches, Summer Itch and Tail Itch. Apply to infected area three times a week.

Active Ingredients

Menthol 1.27%, Chloroxylenol 0.50%, Iodine 0.02%. Inactive ingredients: absinthium oil, acetone, blue 1, plant extracts of calendula, echinacca and wormwood; potassium iodide, thymol, water, yellow 6.

Caution

Keep out of the reach of children. Replace cap firmly. For external use on livestock only. Avoid contact with eyes or mucous membranes. Do not apply to irritated skin. If excessive irritation develops, discontinue use and consult a veterinarian. In long standing cases or those not responding to treatment, or in case of puncture or deep wounds, consult a veterinarian.

If you rub, don't wrap.

Danger

Extremely flammable! Keep away from fire, sparks and heated surfaces.

Distributed by:
W.F. Young, Inc.
E. Longmeadow, MA 01028 U.S.A.

PRINCIPAL DISPLAY PANEL - 946 mL Bottle Label

ABSORBINE ®

VETERINARY
LINIMENT

TOPICAL ANALGESIC
& ANTISEPTIC

Sore Muscle & Joint Pain Relief
Stimulates Circulation to Speed Healing

CLASSIC HERBAL FORMULA
• SINCE 1892 •

32 fl oz (946 mL)